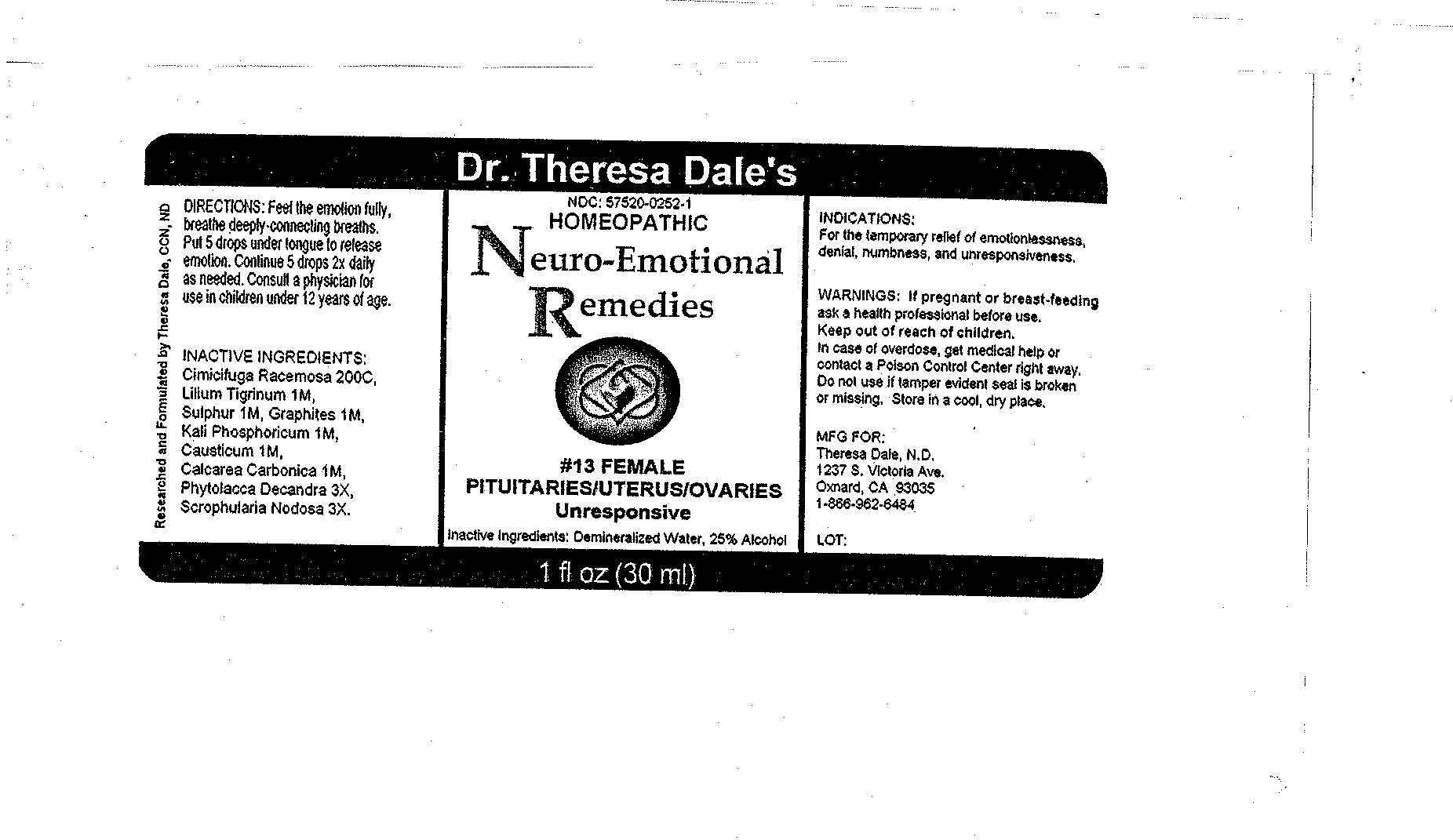 DRUG LABEL: 13 Female 
NDC: 57520-0252 | Form: LIQUID
Manufacturer: Apotheca Company
Category: homeopathic | Type: HUMAN OTC DRUG LABEL
Date: 20100806

ACTIVE INGREDIENTS: PHYTOLACCA AMERICANA ROOT 3 [hp_X]/1 mL; SCROPHULARIA NODOSA 3 [hp_X]/1 mL; BLACK COHOSH 200 [hp_C]/1 mL; LILIUM TIGRINUM 1 [hp_M]/1 mL; SULFUR 1 [hp_M]/1 mL; GRAPHITE 1 [hp_M]/1 mL; POTASSIUM PHOSPHATE, DIBASIC 1 [hp_M]/1 mL; CAUSTICUM 1 [hp_M]/1 mL; OYSTER SHELL CALCIUM CARBONATE, CRUDE 1 [hp_M]/1 mL
INACTIVE INGREDIENTS: WATER; ALCOHOL

#13 Female

ACTIVE INGREDIENT

ACTIVE INGREDIENTS: Phytolacca decandra 3X, Scrophularia nodosa 3X, Cimicifuga racemosa 200C, Lilium tigrinum 1M, Sulphur 1M, Graphites 1M, Kali phosphoricum 1M, Causticum 1M, Calcarea carbonica 1M.

PURPOSE

INDICATIONS: For the temporary relief of emotionlessness, denial, numbness, and unresponsiveness.

WARNINGS

WARNINGS: If pregnant or breast-feeding, ask a health professional before use.

Keep out of reach of children. In case of overdose, get medical help or contact a Poison Control Center right away.

Do not use if tamper evident seal is broken or missing. Store in a cool, dry place.

DOSAGE AND ADMINISTRATION

DIRECTIONS: Feel the emotion, breathe deeply-connecting breaths. Put 5 drops under tongue to release emotion. Continue 5 drops 2x daily as needed. Consult a physician for use in children under 12 years of age.

INACTIVE INGREDIENTS: Demineralized water, 25% Alcohol.

QUESTIONS

MFG FOR:

Theresa Dale, N.D.

1237 S. Victoria Ave.

Oxnard, CA 93035

1-866-962-6484

PACKAGE LABEL

Dr. Theresa Dale's

HOMEOPATHIC

Neuro-Emotional Remedies

#13 FEMALE

PITUITARIES/UTERUS/OVARIES

Unresponsive

1 fl oz (30 ml)